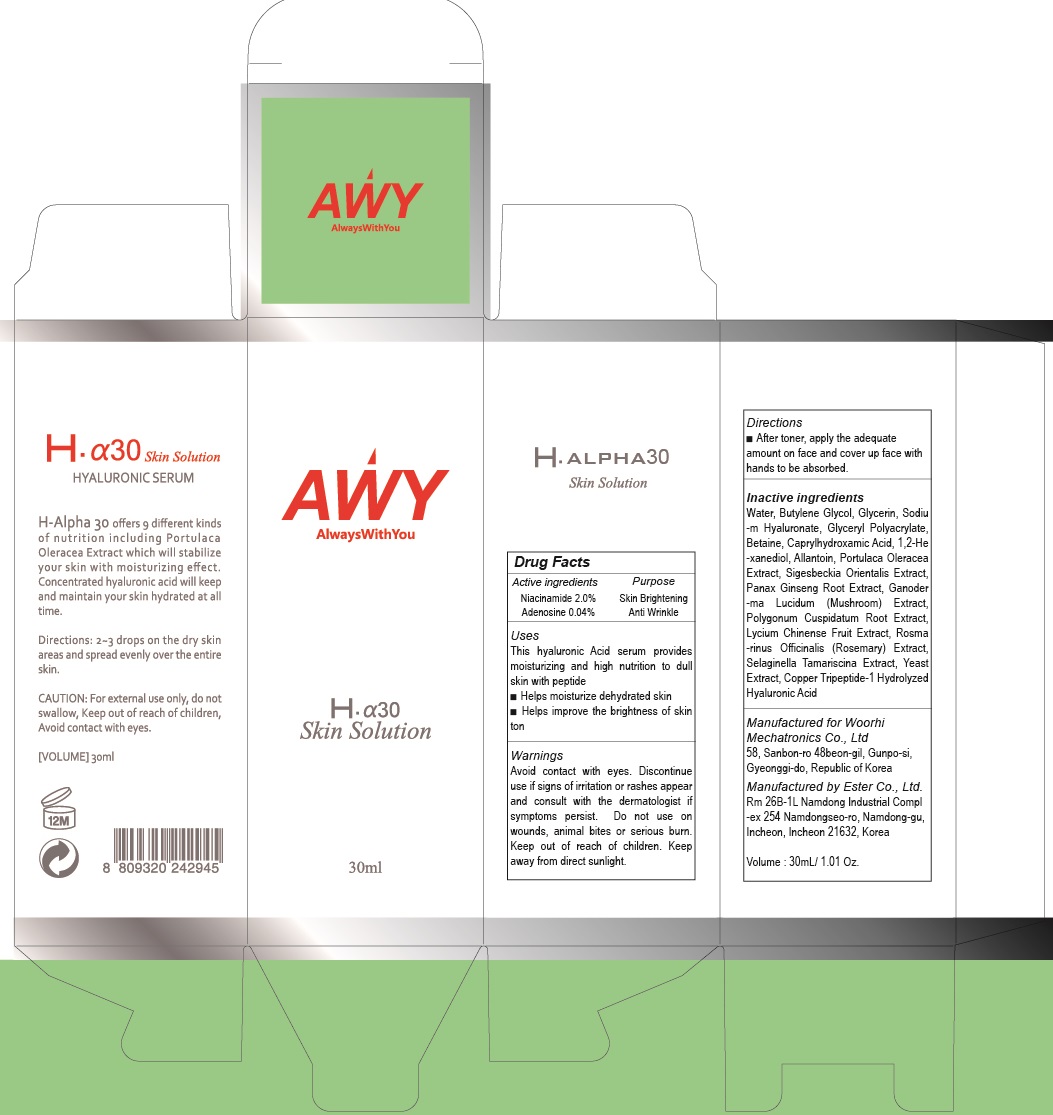 DRUG LABEL: H ALPHA 30 Skin
NDC: 72729-010 | Form: SOLUTION
Manufacturer: Woorhi Mechatronics Co., Ltd.
Category: otc | Type: HUMAN OTC DRUG LABEL
Date: 20181203

ACTIVE INGREDIENTS: Niacinamide 0.60 g/30 mL; Adenosine 0.012 g/30 mL
INACTIVE INGREDIENTS: Water; Butylene Glycol

ACTIVE INGREDIENT

Active Ingredient: Niacinamide 2.0%, Adenosine 0.04%

INACTIVE INGREDIENT

Inactive ingredients:

Water, Butylene Glycol, Glycerin, Sodium Hyaluronate, Glyceryl Polyacrylate, Betaine, Caprylhydroxamic Acid, 1,2-Hexanediol, Allantoin, Portulaca Oleracea Extract, Sigesbeckia Orientalis Extract, Panax Ginseng Root Extract, Ganoderma Lucidum (Mushroom) Extract, Polygonum Cuspidatum Root Extract, Lycium Chinense Fruit Extract, Rosmarinus Officinalis (Rosemary) Extract, Selaginella Tamariscina Extract, Yeast Extract, Copper Tripeptide-1 Hydrolyzed Hyaluronic Acid

PURPOSE

Purpose: Skin Brightening, Anti Wrinkle

WARNINGS

Avoid contact with eyes.

Discontinue use if signs of irritation or rashes appear and consult with the dermatologist if symptoms persist.

Do not use on wounds, animal bites or serious burn.

Keep out of reach of children.

Keep away from direct sunlight.

KEEP OUT OF REACH OF CHILDREN

Uses

This hyaluronic Acid serum provides moisturizing and high nutrition to dull skin with peptide

■ Helps moisturize dehydrated skin

■ Helps improve the brightness of skin tone

Directions

After toner, apply the adequate amount on face and cover up face with hands to be absorbed